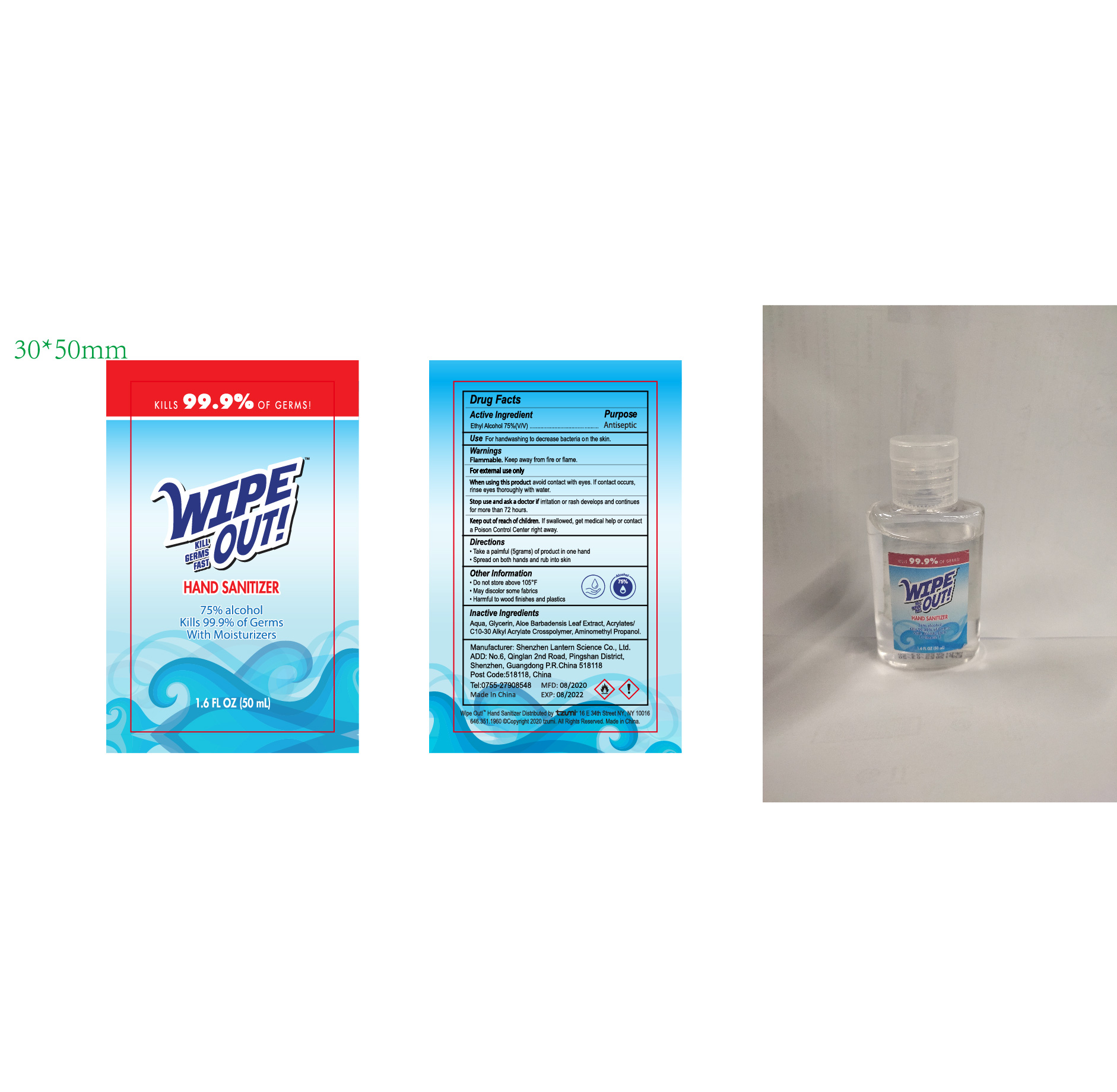 DRUG LABEL: WIPEOUT hand sanitizer 50ml
NDC: 54860-295 | Form: LIQUID
Manufacturer: Shenzhen Lantern Science Co.,Ltd.
Category: otc | Type: HUMAN OTC DRUG LABEL
Date: 20200830

ACTIVE INGREDIENTS: ALCOHOL 75 mL/100 mL
INACTIVE INGREDIENTS: CARBOMER INTERPOLYMER TYPE A (55000 CPS) 0.32 mL/100 mL; WATER 23.96 mL/100 mL; AMINOMETHYLPROPANOL 0.12 mL/100 mL; GLYCERIN 0.5 mL/100 mL; ALOE VERA LEAF 0.1 mL/100 mL

WIPEOUT hand sanitizer 50ml

Active Ingredient

Active Ingredients Purpose

Ethyl Alcohol 75% Antiseptic

Warning

flammable,keep away from heat and flame.

For external use only.

WARNINGS AND PRECAUTIONS

For external use only.

Flammable, keep away from heat and flame.

STOP USE

Discontinue if skin becomes irritated and ask a doctor .

Keep out of reach of children. In case of accidental ingestion, seek professional assistance or contact a poson control center immediately.

Inactive ingredients

Aqua(water),Glycerin,Aloe Barbadensis Leaf Extract,Acrylates/C10-30 Alkyl Acrylate Crosspolymer,Aminomethyl Propanol

Directions

Take a palmful(5 grams) of product in one hand.

Spread on both hands and rub into skin.

When using this product

keep out of eyes. In case of contact with eyes, flush thoroughly with water.

Do not inhale or ingest.

Avoid contact with broken skin.

Other information

Do not store above 105F.

May discolor some fabrics.

Harmful to wood finishes and plastics.

When using this product

avoid contact with eyes,if contact occurs,rinse eyes thoroughly with water.

Keep out of reach of children

If swallowed,get medical help or contact a Poison Control Center right away.

stop use and ask a doctor if irritation or rash develops and continues for more than 72 hours.

Use

For handwashing to decrease bacteria on the skin.

OTHER SAFETY INFORMATION

Do not store above105℉

May discolor some fabrics

Harmful to wood finishes and plastics.

dosage

take a palmful(5 grams) of product in one hand.

spread on both hands and rub into skin.